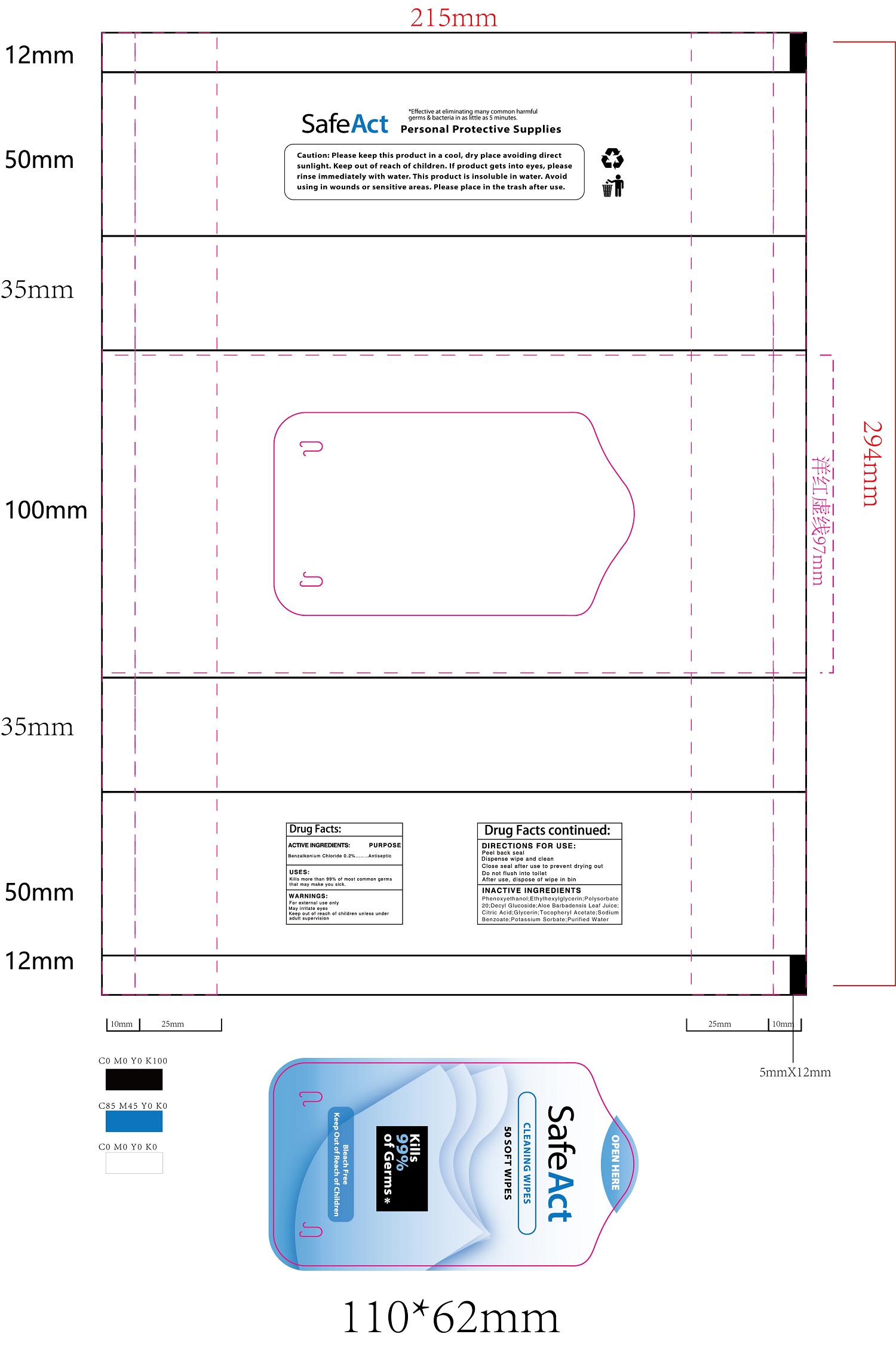 DRUG LABEL: CLEANING WIPES
NDC: 78870-900 | Form: CLOTH
Manufacturer: AMERICAN EXCHANGE TIME LLC
Category: otc | Type: HUMAN OTC DRUG LABEL
Date: 20200609

ACTIVE INGREDIENTS: BENZALKONIUM CHLORIDE 0.1 g/100 g
INACTIVE INGREDIENTS: PHENOXYETHANOL; DECYL GLUCOSIDE; ALOE VERA LEAF; POTASSIUM SORBATE; ALPHA-TOCOPHEROL ACETATE; WATER; CITRIC ACID MONOHYDRATE; ETHYLHEXYLGLYCERIN; SODIUM BENZOATE; GLYCERIN; POLYSORBATE 20

78870-900 clean wipes 0.2% Benzalkonium Chloride

Active Ingredient

Benzalkonium Chloride 0.2 %

Purpose

Antiseptic

USE

Kills more than 99% of most common germs
that may make you sick.

Warning

For external use only
May irritate eyes
Keep out of reach of children unless under
adult supervision

Keep out of reach of children unless under
adult supervision

Directions

Peel back seal
Dispense wipe and clean
Close seal after use to prevent drying out
Do not flush into toilet
After use, dispose of wipe in bin

Inactive ingredients

Phenoxyethanol; Ethylhexylglycerin;P olysorbate
20;DecyI Glucoside;Aloe Barbadensis Leaf Juice;
Citric Acid;Glycerin;TocopheryI Acetate;Sodium
Benzoate;Potassium Sorbate;Purified Water